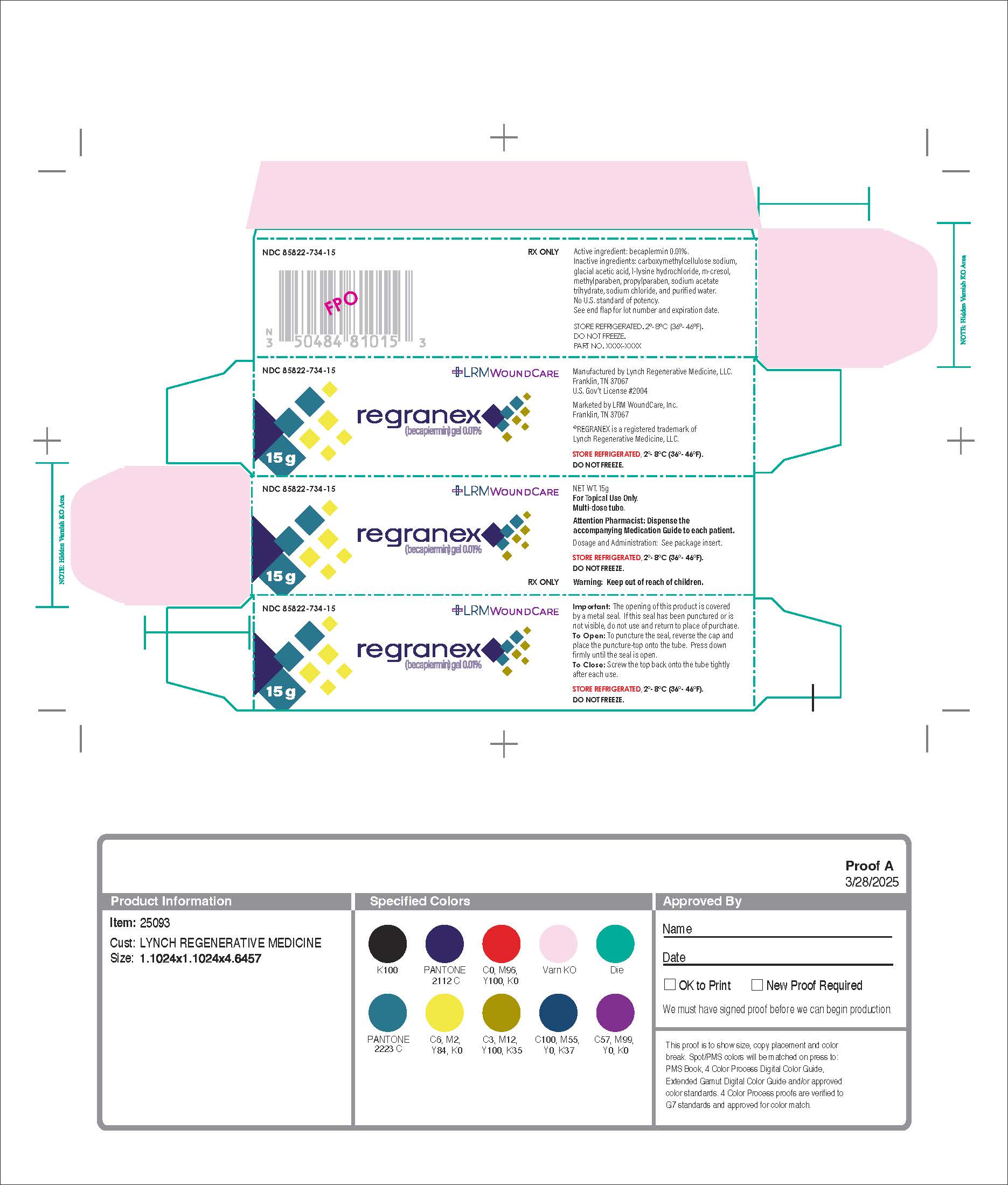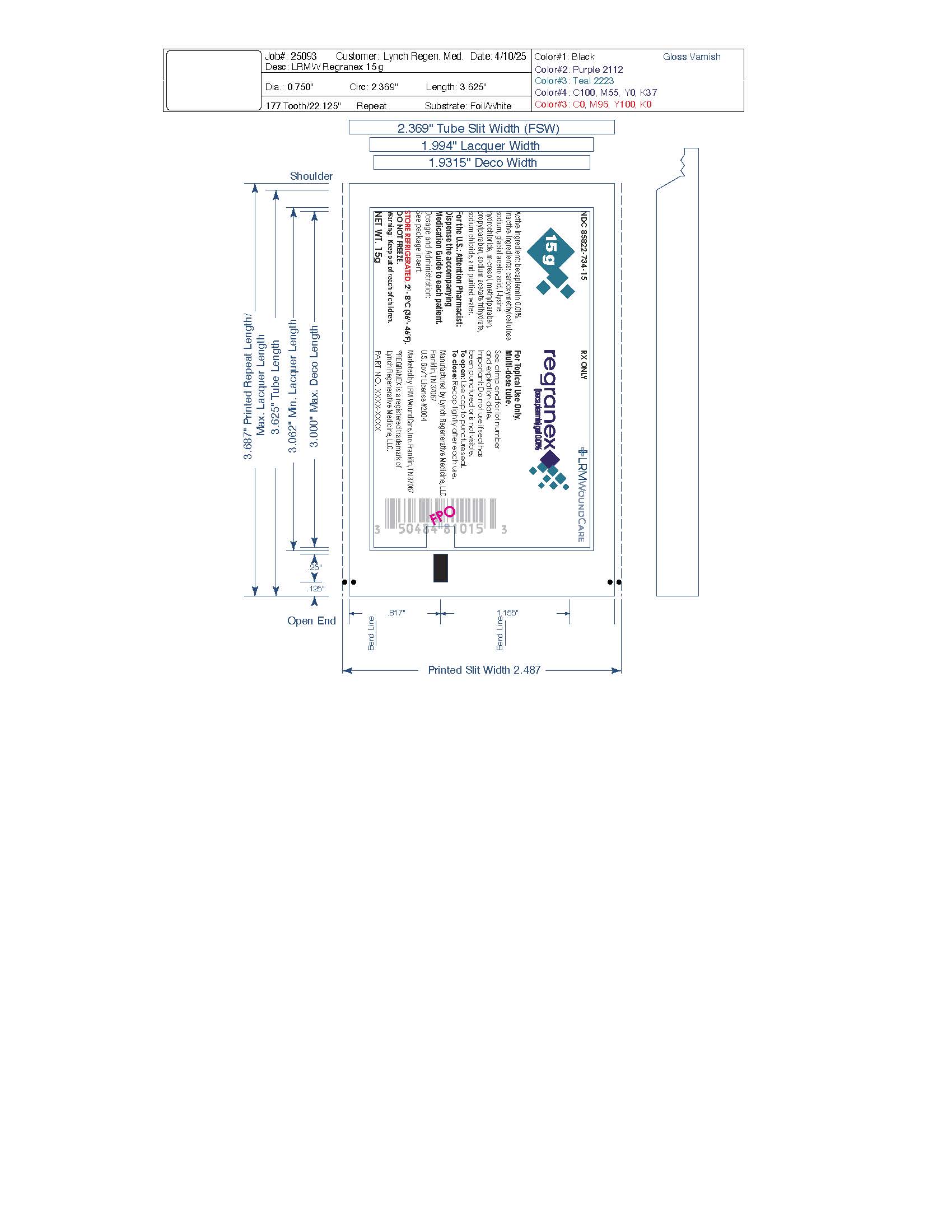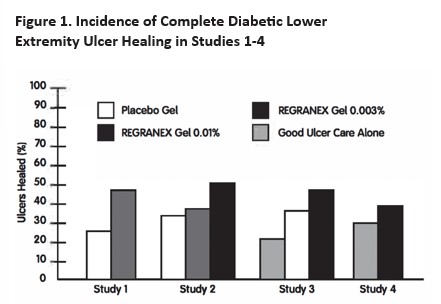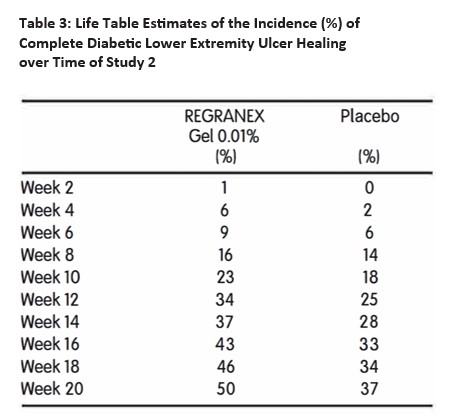 DRUG LABEL: Regranex Gel 0.01%
NDC: 85822-734 | Form: GEL
Manufacturer: Lynch Regnerative Medicine
Category: prescription | Type: HUMAN PRESCRIPTION DRUG LABEL
Date: 20250613

ACTIVE INGREDIENTS: BECAPLERMIN 0.1 mg/1 g

HIGHLIGHTS OF PRESCRIBING INFORMATION

These highlights do not include all the information needed to use REGRANEX®gel safely and effectively.
See full prescribing information for REGRANEX gel.
REGRANEX (becaplermin) gel, for topical use
Initial U.S. Approval: 1997

RECENT MAJOR CHANGES

Boxed Warning, increased rate of cancer mortality (5.11) Removed 11/2018

Warnings and Precautions, cancer mortality (5.11) Removed 11/2018

Revised inactive ingredient names Revised 11/2022

Indications and Usage

REGRANEX is a human platelet-derived growth factor indicated for the treatment of lower extremity diabetic neuropathic ulcers that extend into the subcutaneous tissue or beyond and have an adequate blood supply. REGRANEX is indicated as an adjunct to, and not a substitute for, good ulcer care practices. (1)

Limitations of Use:

The efficacy of REGRANEX has not been established for the treatment of pressure ulcers and venous stasis ulcers. (1)
The effects of REGRANEX on exposed joints, tendons, ligaments, and bone have not been established in humans. (1)
REGRANEX is not intended to be used in wounds that close by primary intention. (1)

Dosage and Administration

- For topical use; not for oral, ophthalmic or intravaginal use. (2)
- To calculate the length of REGRANEX to apply, measure the greatest length of the ulcer by greatest width of the ulcer in either inches or centimeters. (2)

Formula to Calculate Length of Gel to Be Applied Daily

Tube Size Formula

15 g Tube Inches: ulcer length x ulcer width x 0.6

15 g Tube Centimeters: ulcer length x ulcer width + 4

Dosage Form and Strengths

Gel: 0.01% (31)

Contraindications

Known neoplasm(s) at the site(s) of application. (4)

Warnings and Precautions

Malignancies distant from the site of application have been reported in both a clinical study and in postmarketing use. (5.1)

The benefits and risks of REGRANEX treatment should be carefully evaluated before prescribing in patients with known malignancy. (5.1)

ADVERSE REACTIONS

Erythematous rashes occurred in 2% of patients treated with REGRANEX. (6.1)

To report suspected ADVERSE REACTIONS contact FDA at 1-800-332-1088 or www.fda.gov/medwatch, or Smith & Nephew, Inc. at 1-800-441-8227.

See 17 for Patient Counseling Information and Medication Guide.

FULL PRESCRIBING INFORMATION

RECENT MAJOR CHANGES

Boxed Warning, increased rate of cancer mortality (5.11) Removed 11/2018

Warnings and Precautions, cancer mortality (5.11) Removed 11/2018

Revised inactive ingredient names Revised 11/2022

Indications and Usage

REGRANEX is indicated for the treatment of lower extremity diabetic neuropathic ulcers that extend into the subcutaneous tissue or beyond and have an adequate blood supply, when used as an adjunct to, and not a substitute for, good ulcer care practices including initial sharp debridement, pressure relief and infection control.

Limitations of Use:

The efficacy of REGRANEX has not been established for the treatment of pressure ulcers and venous stasis ulcers [see Clinical Studies /14.2)1 and has not been evaluated for the treatment of diabetic neuropathic ulcers that do not extend through the dermis into subcutaneous tissue [Stage I or 11, International Association of Enterostomal Therapy (IAET) staging classification] or ischemic diabetic ulcers.

The effects of becaplermin on exposed joints, tendons, ligaments, and bone have not been established in humans [see Nonclinical Toxicology /13.2)].

REGRANEX is not intended to be used in wounds that close by primary intention.

Dosage and Administration

REGRANEX is for topical use; it is not for oral, ophthalmic or intravaginal use.

The amount of REGRANEX to be applied depends upon the size of the ulcer area. To calculate the length of gel to apply lo the ulcer, measure the greatest length of the ulcer by the greatest width of the ulcer in either inches or centimeters. To calculate the length of gel in inches, use the formula shown below in Table 1, and to calculate the length of gel in centimeters, use the formula shown below in Table 2.

Table 1: Formula to Calculate Length of Gel in

Inches to Be Applied Daily

INCHES

–—————————————

Tube Size Formula

———————————————————————————

15 g tube length x width x 0.6

Using the calculation, each square inch of ulcer surface will

require approximately 2/3 inch length of gel squeezed from

a 15 g tube. For example, if the ulcer measures 1 inch by

2 inches, then a 1 l / 4 inch length of gel should be used for

15 g tubes 11 x 2 x 0.6 = 1 1/4).

Table 2: Formula to Calculate Length of Gel in

Centimeters to Be Applied Daily

CENTIMETERS

–—————————————

Tube Size Formula

———————————————————————————

15 g tube length x width + 4

Using the calculations for ulcer size in centimeters, each square centimeter of ulcer surface will require approximately a 0.25 centimeter length of gel squeezed from a 15 g tube. For example, if the ulcer measures 4 cm by 2 cm, then a 2 cm length of gel should be used for a 15 g tube [14 x 21 + 4 = 21. The amount of REGRANEX to be applied should be recalculated by the physician or wound caregiver at weekly or biweekly intervals depending on the rate of change in ulcer area. The weight of REGRANEX from 15 g tubes is 0.65g per inch length and 0.25 g per centimeter length.

To apply REGRANEX, the calculated length of gel should be squeezed on to a ciean measuring surface, e.g., wax paper, and measured to the correct length with a ruler. The measured REGRANEX is transferred from the clean measuring surface using an application aid and then spread over the entire cleaned ulcer area to yield a thin continuous layer of approximately 1/16 of an inch thickness. The site(s) of application should then be covered by a saline moistened gauze dressing and left in place for approximately 12 hours. The dressing should then be removed and the ulcer rinsed with saline or water to remove residual gel and covered again with a moist primary dressing (without REGRANEX gel) for the remainder of the day. REGRANEX should be applied once daily to the ulcer until complete healing has occurred. If the ulcer does not decrease in size by approximately 30% after 10 weeks of treatment or complete healing has not occurred in 20 weeks, continued treatment with REGRANEX should be reassessed. The step-by-step instructions for applying REGRANEX in a home care setting can be found in the FDA-approved Instructions for Use.

Dosage Form and Strengths

Gel: 0.01%; Clear, colorless to straw-colored.

Contraindications

REGRANEX is contraindicated in patients with known neoplasm(s) at the site(s) of application.

Warnings and Precautions

5.1 Risk of Cancer

REGRANEX contains becaplermin, a recombinant human platelet-derived growth factor, which promotes cellular proliferation and angiogenesis [see Clinical Pharmacology /12.1)]. Malignancies distant from the site of application have occurred in REGRANEX users in a clinical study and in postmarketing use {see Adverse Reactions /6.1) and Clinical Studies /14.3)].

The benefits and risks of REGRANEX treatment should be carefully evaluated before prescribing in patients with known malignancy.

5.2 Application Site Reactions

If application site reactions occur, the possibility of sensitization or irritation caused by parabens or m-cresol should be considered. Consider interruption or discontinuation and further evaluation (e.g. patch testing) as dictated by clinical circumstances.

ADVERSE REACTIONS

6.1 Clinical Trials Experience

Because clinical trials are conducted under widely varying conditions, adverse reaction rates observed in the clinical trials of a drug cannot be directly compared to rates in the clinical trials of another drug and may not reflect the rates observed in practice.

- In clinical trials, erythematous rashes occurred in 2% of subjects treated with REGRANEX (and good ulcer care) or placebo land good ulcer care), and none in subjects receiving good ulcer care alone. Subjects treated with REGRANEX did not develop neutralizing antibodies against becaplermin.
- In a retrospective follow-up study of 491 of 651 subjects (75%) from two randomized, controlled trials of another formulation of becaplermin gel 0.01%, the subjects were followed for a median of approximately 20 months to evaluate safety and recurrence of healed diabetic lower extremity ulcers. Eight of 291 subjects (2.7%) from the becaplermin gel group and two of 200 subjects (1%) from the vehicle/ standard of care group were diagnosed with cancers during the follow-up period, a relative risk of 2.7 (95% confidence interval [Cll, 0.6-12.8). The types of cancers varied and all were remote from the treatment site [see Warnings and Precautions (5.1)].

6.2 Postmarketing Experience

Because post-approval adverse reactions are reported voluntarily from a population of uncertain size, it is not always possible to reliably estimate their frequency or establish a causal relationship to the drug. The following adverse reactions have been identified during post approval use of REGRANEX.

- Increased rate of death from systemic malignancies in patients dispensed 3 or more tubes of REGRANEX was observed in one of three retrospective postmarketing studies {see Clinical Studies /14.3)].
- Burning sensation and erythema at the site of application have been reported.

To report SUSPECTED ADVERSE REACTIONS contact FDA at 1-800-322-1088 or www.fda.gov/medwatch, or Smith & Nephew, Inc. at 1-800-441-8227.

Drug Interactions

It is not known if REGRANEX interacts with other topical medications applied to the ulcer site. The use of REGRANEX with other topical drugs has not been studied.

Use in Specific Populations

8.1 Pregnancy

Risk Summary

There are no available data on REGRANEX use in pregnant women to inform a drug-associated risk of major birth defects, miscarriage, or adverse maternal or fetal outcomes. Animal reproduction studies have not been conducted with REGRANEX.

The background risk of major birth defects and miscarriage for the indicated population is unknown. In the U.S. general population, the estimated background risk of major birth defects and miscarriage in clinically recognized pregnancies is 2% to 4% and 15% to 20%, respectively.

8.2 Lactation

There are no data on the presence of becaplermin in human milk, the effects on the breastfed infant or the effects on milk production after topical application of REGRANEX to lactating women. The developmental and health benefits of breastfeeding should be considered along with the lactating woman's clinical need for REGRANEX and any potential adverse effects on the breastfed child from becaplermin.

8.4 Pediatric Use

Safety and effectiveness of REGRANEX in pediatric patients below the age of 16 years have not been established.

8.5 Geriatric Use

Among subjects receiving any dose of REGRANEX in clinical studies of diabetic lower extremity ulcers, 150 subjects were 65 years of age and over. No overall differences in safety or effectiveness were observed between these subjects and younger subjects. The number of subjects aged 75 and older was insufficient ln=341 to determine whether they respond differently from younger subjects.

Overdosage

here are no data on the effects of REGRANEX overdose.

Description

REGRANEX contains becaplermin, a recombinant human platelet-derived growth factor, for topical administration. Becaplermin is produced by recombinant DNA technology by insertion of the gene for the B chain of platelet-derived growth factor IPDGF) into the yeast, Saccharomyces cerevisiae.

Becaplermin has a molecular weight of approximately 25 kD and is a homodimer composed of two identical polypeptide chains that are bound together by disulfide bonds. REGRANEX is a non-sterile, low bioburden, preserved, sodium carboxymethylcellulose-based (CMC) topical gel, containing the active ingredient becaplermin and the following inactive ingredients: carboxymethylcellulose sodium, acetic acid, lysine hydrochloride, metacresol, methylparaben, propylparaben, sodium acetate, sodium chloride, and purified water. Each gram of REGRANEX contains 100 mcg of becaplermin.

Clinical Pharmacology

12.1 Mechanism of Action

REGRANEX has biological activity similar to that of endogenous platelet-derived growth factor, which includes promoting the chemotactic recruitment and proliferation of cells involved in wound repair and enhancing the formation of granulation tissue.

12.2 Pharmacodynamics

Clinical pharmacodynamic studies have not been conducted.

12.3 Pharmacokinetics

Ten subjects with Stage Ill or IV [as defined in the International Association of Enterostomal Therapy IIAETI guide to chronic wound staging] lower extremity diabetic ulcers received topical applications of becaplermin gel 0.01% at a dose range of 0.32-2.95 mcg/kg 17 mcg/cm2) daily for 14 days. Six subjects had non-quantifiable PDGF levels at baseline and throughout the study, two subjects had PDGF levels at baseline which did not increase substantially, and two subjects had PDGF levels that increased sporadically above their baseline values during the 14-day study period.

NONCLINICAL TOXICOLOGY

13.1 Carcinogenesis, Mutagenesis, Impairment of Fertility

Becaplermin was not genotoxic in a battery of in vitro assays (including those for bacterial and mammalian cell point mutation, chromosomal aberration, and DNA damage/repair). Becaplermin was also not mutagenic in an in vivo assay for the induction of micronuclei in mouse bone marrow cells. Carcinogenesis and reproductive toxicity studies have not been conducted with REGRANEX.

13.2 Animal Toxicology and/or Pharmacology

In nonclinical studies, rats injected at the metatarsals with 3 orl0 mcg/site (approximately 60 or 200 mcg/kg) of becaplermin every other day for 13 days displayed histological changes indicative of accelerated bone remodeling consisting of periosteal hyperplasia and subperiosteal bone resorption and exostosis. The soft tissue adjacent to the injection site had fibroplasia with accompanying mononuclear cell infiltration reflective of the ability of PDGF to stimulate connective tissue growth.

CLINICAL STUDIES

14.1 Efficacy in Diabetic Lower Extremity Ulcers

The effects of REGRANEX on the incidence of and time to complete healing in lower extremity diabetic neuropathic ulcers were assessed in four randomized controlled studies (Studies 1-4). Of 922 subjects studied, 478 received either REGRANEX 0.003% or 0.01%. All study participants had lower extremity diabetic neuropathic ulcers that extended into the subcutaneous tissue or beyond [Stages Ill and IV of the International Association of Enterostomal Therapy (IAET) guide to chronic wound staging]. Ninety-three percent of the subjects enrolled in these four trials had foot ulcers. The remaining 7% of the subjects had ankle or leg ulcers. The diabetic ulcers were of at least 8 weeks duration and had an adequate blood supply (defined as TcpO2 > 30 mm Hg). In the four trials, 95% of the ulcers measured in area up to 10 cm^2, and the median ulcer size at baseline ranged from 1.4 cm^2 to 3.5 cm^2.

All treatment groups received a program of good ulcer care consisting of initial complete sharp debridement. A non-weight-bearing regimen, systemic treatment for wound-related infection if present, moist saline dressings changed twice a day, and additional debridement as necessary. REGRANEX 0.003% or 0.01% or placebo was applied once a day and covered with a saline moistened dressing. After approximately 12 hours, the gel was gently rinsed off and a saline moistened dressing was then applied for the remainder of the day. Subjects were treated until complete healing, or for a period of up to 20 weeks. Subjects were considered a treatment failure if their ulcer did not show an approximately 30% reduction in initial ulcer area after eight to ten weeks of therapy.

Results of the primary endpoints from 4 independent studies, shown as incidence of complete ulcer closure within 20 weeks, for all treatment arms are given in Figure 1. In each study, REGRANEX in conjunction with good ulcer care was compared to placebo gel plus good ulcer care or good ulcer care alone.

In Study 1, a multicenter, double-blind, placebo-controlled trial of 118 subjects, the incidence of complete ulcer closure for REGRANEX 0.003% (n=61) was 48% versus 25% for placebo gel (n=57; p=0.02, logistic regression analysis).

In Study 2, a multicenter, double-blind, placebo-controlled trial of 382 subjects, the incidence of complete ulcer closure for REGRANEX 0.01% (n=123I was 50% versus 36% for REGRANEX 0.003% (n=132) and 35% for placebo gel (n=127I. Only REGRANEX 0.01% was significantly different from placebo gel (p=0.01, logistic regression analysis).

The primary goal of Study 3, a multicenter controlled trial of 172 subjects, was to assess the safety of vehicle gel (placebo; n=70I compared to good ulcer care alone (n=681. The study included a small (n=34) REGRANEX 0.01% arm. Incidences of complete ulcer closure were 44% for REGRANEX, 36% for placebo gel and 22% for good ulcer care alone.

In Study 4, a multicenter, evaluator-blind, controlled trial of 250 subjects, the incidences of complete ulcer closure in the REGRANEX 0.01% arm (n=128I (36%) and good ulcer care alone (n=122} (32%) were not statistically different.

Figure 1. Incidence of Complete Diabetic Lower

Extremity Ulcer Healing in Studies 1-4

In general, where REGRANEX was associated with higher

incidences of complete ulcer closure, differences in the

incidence first became apparent after approximately 10

weeks and increased with continued treatment (Table 3).

Table 3: Life Table Estimates of the Incidence (%) of

Complete Diabetic Lower Extremity Ulcer Healing

over Time of Study 2

In a 3-month follow-up period where no standardized

regimen of preventative care was utilized, the incidence of

ulcer recurrence was approximately 30% in all treatment

groups, demonstrating that the durability of ulcer closure

was comparable in all treatment groups.

14.2 Lack of Efficacy in Pressure Ulcers and Venous Stasis Ulcers

In a randomized, double-blind study of REGRANEX 1100 mcg/g once daily for 16 weeks) in subjects with Stage Ill or IV pressure ulcers, the incidence of complete ulcer closure was 15% (28/189) in the REGRANEX group and 12% (22/190) in the vehicle control group. This difference was not statistically significant.

In two small, randomized, double-blinded studies of REGRANEX 1100 mcg/g once daily for 16 weeks) in subjects with venous stasis ulcers, the combined incidence of complete ulcer closure was 46% (30/65) in the REGRANEX group and 39% (26/67) in the vehicle control group. This difference was not statistically significant.

14.3 Observational Studies to Evaluate Cancer Development and Mortality

The observational studies described below do not involve random allocation of treatments. They are susceptible to bias and confounding. A retrospective study using medical claims database to assess cancer incidence with up to 6 years of follow-up observed development of 28 cancers and 8 cancer deaths in the REGRANEX exposed cohort (n = 1,622) and 43 cancers and 8 cancer deaths in the matched comparator cohort not exposed to REGRANEX (n = 2,809). The rate ratio for incident cancer comparing the REGRANEX-exposed cohort to the unexposed comparator cohort was 1.2 (95% Cl, 0.7 -1.9). The rate ratio for cancer mortality comparing the REGRANEX-exposed cohort to the unexposed comparator cohort was l.8 (95% Cl, 0.7 -4.9). The rate ratio comparing patients exposed to three or more tubes of REGRANEX to those not exposed was 5.2 (95% Cl, 1.6 -17.61 [see Adverse Reactions /6.2/J. A retrospective study using medical claims from the Veteran Affairs health care database with up to 11 years of follow-up among patients without prior cancer observed 197 cancer deaths in the REGRANEX exposed cohort (n = 6,429) and 206 cancer deaths in the matched comparator cohort not exposed to REGRANEX (n = 6,429), resulting in a hazard ratio of 0.9 (95% Cl, 0.8-1.2). The hazard ratio for cancer mortality comparing patients exposed to three or more tubes of REGRANEX to those not exposed was 1.0 (95% Cl, 0.7 -1.5). The hazard ratio for incident cancer in a smaller cohort 11,507 REGRANEX-exposed and 1,507 unexposed patients) comparing patients exposed to REGRANEX to those not exposed was 1.1 (95% Cl, 0.8-1.4). A second retrospective study using medical claims from the Veteran Affairs health care database with up to 11 years of follow-up among patients with prior cancer observed 87 cancer deaths in the REGRANEX-exposed cohort (n = 477) and 340 cancer deaths in the matched comparator cohort not exposed to REGRANEX (n = 1,756), resulting in a hazard ratio of 0.9 (95% Cl, 0.7-1.2). The hazard ratio for cancer mortality comparing patients exposed to three or more tubes of REGRANEX to those not exposed was 0.9 (95% Cl, 0.6 -1.2).

HOW SUPPLIED/STORAGE AND HANDLING

REGRANEX (0.01%) is clear, colorless to straw-colored and is available in multi-use tubes in the following size:

15 g tube NOC 50484-810-15

Store refrigerated at 2° - 8° C (36 ° - 46 ° F). Do not freeze.

PATIENT COUNSELING INFORMATION

- Advise patients and caregivers to read the FDA-approved patient labeling (Medication Guide and Instructions for Use) and follow the step-by-step instructions for REGRANEX application in the Instructions for Use.
- Counsel patients to review and discuss any questions or concerns with their healthcare provider before starting REGRANEX and at regular intervals while receiving REGRANEX.
- Advise patients that it is important to use REGRANEX together with a good ulcer care program, including a strict non-weight-bearing program.
- Advise patients to store REGRANEX in the refrigerator and not to freeze REGRANEX.

MEDICATION GUIDE REGRANEX

Important: REGRANEX is for use on the skin only (topical). Do not use REGRANEX near or in your mouth, eyes, or vagina.

What is the most important information I should know about REGRANEX?

REGRANEX may cause serious side effects, including:

Risk of cancer. Cancers have happened in areas away from the REGRANEX application site. You and your healthcare provider should carefully consider whether you will use REGRANEX if you have cancer.

What is REGRANEX?

REGRANEX is a prescription medicine that is used with good ulcer care practice for the treatment of diabetic sores (ulcers) of your legs or feet that are deeper than just your skin, in people who have good blood supply to the legs and feet.

It is not known if REGRANEX is effective for the treatment of pressure ulcers or ulcers that are due to poor blood flow (circulation).

It is not known if REGRANEX is safe and effective in children under 16 years of age.

Who should not use REGRANEX?

Do not use REGRANEX if you have a cancer at the application site.

Before using REGRANEX, tell your healthcare provider about all of your medical conditions, including if you:

- have cancer.
- are pregnant or plan to become pregnant. It is not known if REGRANEX will harm your unborn baby.
- are breastfeeding or plan to breastfeed. It is not known if REGRANEX passes into your breast milk. Talk to your healthcare provider about the best way to feed your baby during treatment with REGRANEX.

Tell your healthcare provider about all the medicines you take, including prescription and over-the-counter medicines, vitamins, and herbal supplements.

How should I use REGRANEX?

Read the Instructions for Use for detailed information about the right way to apply REGRANEX.

- Use REGRANEX together with good ulcer care, as prescribed by your healthcare provider. This includes following your healthcare provider's instructions about not putting weight (non-weight bearing) on the affected leg and foot.
- Use REGRANEX exactly as your healthcare provider tells you to use it.
- The amount of REGRANEX you will apply will depend on the size of your ulcer. Your healthcare provider should check the size of your ulcer every 1 to 2 weeks. Your healthcare provider may change the amount of REGRANEX to be applied to your ulcer as the size of your ulcer changes.

What are the possible side effects of REGRANEX?

REGRANEX may cause serious side effects.

- See "What is the most important information I should know about REGRANEX?"
- Application site reactions. Tell your healthcare provider if you have any skin reactions such as burning sensation at the site of application during treatment with REGRANEX. Your healthcare provider may temporarily stop or completely stop treatment with REGRANEX if you have skin reactions.

The most common side effect of REGRANEX is red skin rashes.

Call your doctor for medical advice about side effects. You may report side effects to FDA at 1-800-FDA-1088.

You may also report side effects to Smith & Nephew, Inc. at 1-800-441-8227.

How should I store REGRANEX?

- Store REGRANEX in the refrigerator at 36 °F to 46 °F (2° C to 8° C).
- Do not freeze REGRANEX.
- Do not use REGRANEX after the expiration date on the bottom (sealed end) of the tube.
- Throw away your REGRANEX that is out of date or no longer needed for your treatment.

Keep REGRANEX and all medicines out of the reach of children.

General information about the safe and effective use of REGRANEX

Medicines are sometimes prescribed for purposes other than those listed in a Medication Guide. Do not use REGRANEX for a condition for which it was not prescribed. Do not give REGRANEX to other people, even if they have the same symptoms that you have. It may harm them. You can ask your healthcare provider or pharmacist for information about REGRANEX that is written for health professionals.

What are the ingredients in REGRANEX?

Active ingredient: becaplermin

Inactive ingredients: carboxymethylcellulose sodium, acetic acid, lysine hydrochloride, metacresol, methylparaben, propylparaben, sodium acetate, sodium chloride, and purified water.

INSTRUCTIONS FOR USE REGRANEX

Important: REGRANEX is for use on the skin only (topical). Do not use REGRANEX near or in your mouth, eyes, or vagina.

Read these Instructions for Use before you start using REGRANEX and each time you get a refill. There may be new information. This information does not take the place of talking to your healthcare provider about your medical condition or treatment. Follow your healthcare provider's instructions for measuring and applying REGRANEX.

- Apply REGRANEX one time a day to ulcer area.
- Do not use more than your prescribed dose REGRANEX or apply more often than every 24 hours.
- Do not let the tip of your REGRANEX tube touch the ulcer or any other surface.
- Put the REGRANEX tube in the refrigerator after each use.

Supplies you need to apply REGRANEX:

- Clean cotton swab, tongue depressor or similar application aid
- Ruler or measuring tape
- Clean firm, non-absorbable surface, such as wax paper
- Saline moistened gauze dressing

Step 1. Preparing the REGRANEX dose.

- Wash your hands well before you apply REGRANEX.
- Remove the cap from the REGRANEX tube and use the top of the cap to pierce the foil seal on the top of the tube by pushing or screwing the cap in.
- Carefully measure the amount of REGRANEX that your healthcare provider tells you to use.
- Squeeze the amount of REGRANEX needed for your ulcer on to the clean, firm non-absorbable surface and measure to the correct length with a ruler as prescribed by your healthcare provider.
- Close the REGRANEX tube tightly.

Step 2. Applying REGRANEX.

- Use a clean cotton swab, tongue depressor, or similar application aid to spread the measured amount of REGRANEX in a thin even layer over the ulcer area.
- Cover the application site with a saline moistened gauze dressing.
- Wash your hands well.

Step 3. Removing REGRANEX.

- Remove REGRANEX after 12 hours.
- Wash your hands well.
- Remove the saline moistened gauze dressing.
- Rinse the ulcer with saline or water to remove any REGRANEX gel.
- Cover the ulcer with a new moistened dressing.
- Wash your hands well.

How should I store REGRANEX?

- Store REGRANEX in the refrigerator at 36 °F to 46 °F (2° C to 8° C).
- Do not freeze REGRANEX.
- Do not use REGRANEX after the expiration date on the bottom (sealed end) of the tube.
- Throw away your REGRANEX that is out of date or no longer needed for your treatment.

Keep REGRANEX and all medicines out of the reach of children.